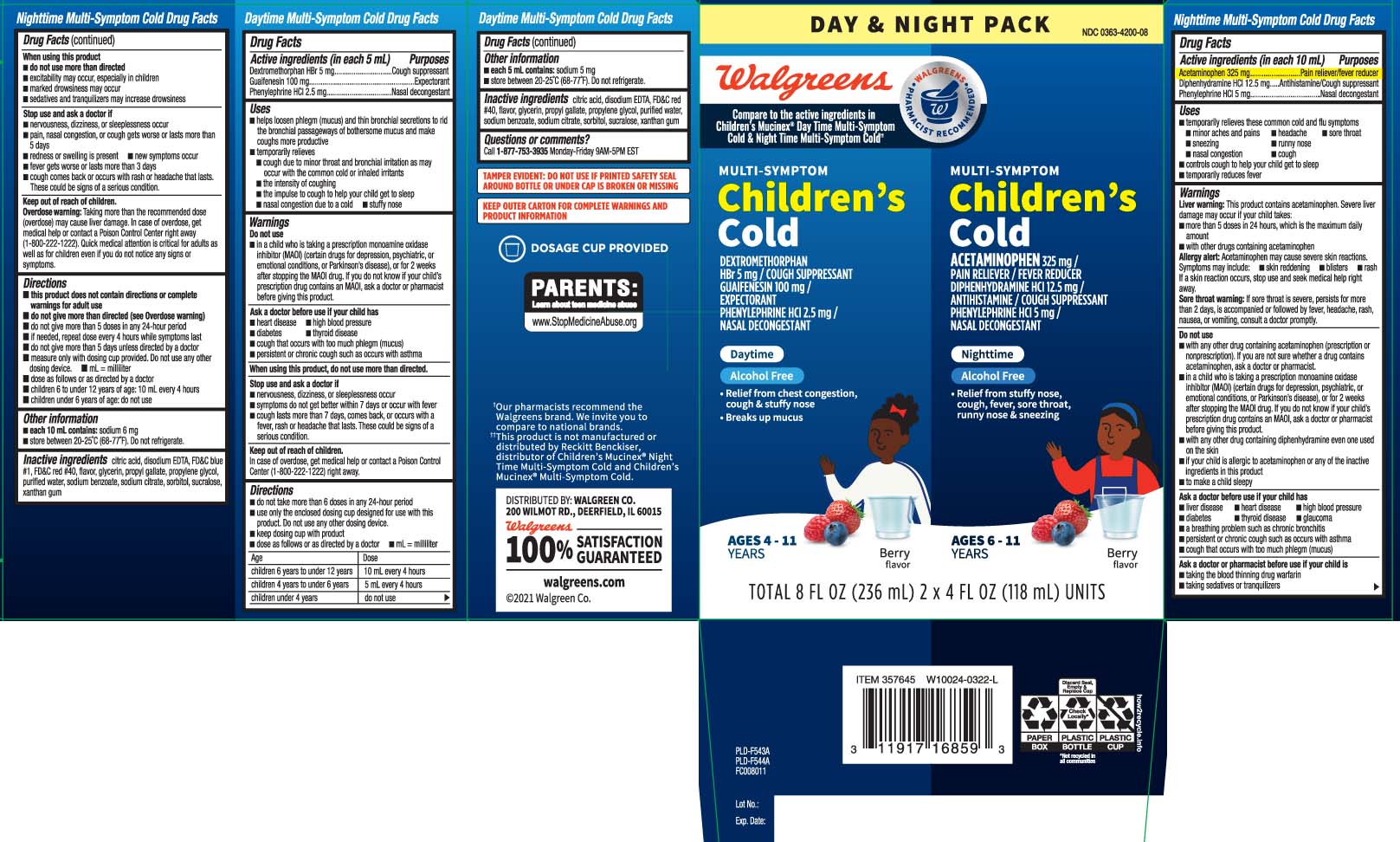 DRUG LABEL: Daytime Nighttime Multi Symptom Cold
NDC: 0363-4200 | Form: KIT | Route: ORAL
Manufacturer: Walgreens
Category: otc | Type: HUMAN OTC DRUG LABEL
Date: 20240621

ACTIVE INGREDIENTS: DEXTROMETHORPHAN HYDROBROMIDE 5 mg/5 mL; PHENYLEPHRINE HYDROCHLORIDE 2.5 mg/5 mL; GUAIFENESIN 100 mg/5 mL; ACETAMINOPHEN 325 mg/10 mL; DIPHENHYDRAMINE HYDROCHLORIDE 12.5 mg/10 mL; PHENYLEPHRINE HYDROCHLORIDE 5 [arb'U]/10 mL
INACTIVE INGREDIENTS: ANHYDROUS CITRIC ACID; EDETATE DISODIUM; FD&C RED NO. 40; GLYCERIN; PROPYLENE GLYCOL; PROPYL GALLATE; WATER; SODIUM BENZOATE; SORBITOL; SUCRALOSE; TRISODIUM CITRATE DIHYDRATE; XANTHAN GUM; ANHYDROUS CITRIC ACID; EDETATE DISODIUM; FD&C BLUE NO. 1; FD&C RED NO. 40; GLYCERIN; PROPYLENE GLYCOL; PROPYL GALLATE; WATER; SODIUM BENZOATE; SORBITOL; SUCRALOSE; TRISODIUM CITRATE DIHYDRATE; XANTHAN GUM

Drug Facts

Active ingredients for Day Time (in each 5 mL)

Dextromethorphan HBr 5 mg

Guaifenesin 100 mg

Phenylephrine HCl 2.5 mg

Active ingredients for Night Time (in each 10 mL)

Acetaminophen 325 mg

Diphenhydramine HCL12.5 mg

Phenylephrine HCL5 mg

Purposes for Day Time

Cough suppressant

Expectorant

Nasal decongestant

Purposes for Night Time

Pain reliever/fever reducer

Antihistamine/Cough suppressant

Nasal decongestant

Uses

Daytime

- helps loosen phlegm (mucus) and thin bronchial secretions to rid the bronchial passageways of bothersome mucus and make coughs more productive
- temporarily relieves
  - cough due to minor throat and bronchial irritation as may occur with the common cold or inhaled irritants
  - the intensity of coughing
  - the impulse to cough to help your child get to sleep
  - nasal congestion due to a cold
  - stuffy nose

Nighttime

- temporarily relieves these common cold and flu symptoms:
  - minor aches and pains
  - headache
  - sore throat
  - sneezing
  - runny nose
  - nasal congestion
  - cough
- controls cough to help your child get to sleep
- temporarily reduces fever

Warnings

Nighttime only

Liver warning: This product contains acetaminophen. Severe liver damage may occur if your child takes:

- more than 5 doses in 24 hours, which is the maximum daily amount
- with other drugs containing acetaminophen

Allergy alert: Acetaminophen may cause severe skin reactions. Symptoms may include:

- skin reddening
- blisters
- rash

If a skin reaction occurs, stop use and seek medical help right away.

Sore throat warning: if sore throat is severe, persists for more than 2 days, is accompanied or followed by fever, headache, rash, nausea, or vomiting, consult a doctor promptly.

Do not use

DAYTIME

- in a child who is taking a prescription monoamine oxidase inhibitor (MAOI) (certan drugs for depression, psychiatric or emotional conditions, or Parkinson's disease), or for 2 weeks after stopping the MAOI drug. If you do not know if your childs prescription drug contains an MAOI, ask a doctor or pharmacist before giving this product.

NIGHTTIME

- with other drug containing acetaminophen (prescription or nonprescription). If you are not sure whether a drug contains acetaminophen, ask a doctor or pharmacist.
- in a child who is taking a prescription monoamine oxidase inhibitor (MAOI) (certain drugs for depression, psychiatric, or emotional conditions, or Parkinson's disease), or for 2 weeks after stopping the MAOI drug. If you do not know if your child's prescription drug contains an MAOI, ask a doctor or pharmacist before giving this product.
- with any other drug containing diphenhydramine even one used on the skin
- if your child is allergic to acetaminophen or any of the inactive ingredients in thia product
- to make a child sleepy

Ask a doctor before use your child has

DAYTIME

- heart disease
- high blood pressure
- diabetes
- thyroid disease
- cough that occurs with too much phlegm (mucus)
- persistent or chronic cough such occurs with asthma

NIGHTTIME

- liver disease
- heart disease
- high blood disease
- diabetes
- thyroid disease
- glaucoma
- a breathing problem such as chronic bronchitis
- persistent or chronic cough such as occurs with asthma
- cough that occurs with too much phlegm (mucus)

Ask a doctor or pharmacist before use if the child is

NIGHTTIME

- taking sedatives or tranquilizers.
- taking the blood thinning drug warfarin

When using this product

Daytime

do not use more than directed.

Nighttime

- do not use more than directed
- excitability may occur, especially in children
- marked drowsiness may ocur
- sedatives and tranquilizers may increase drowsiness

Stop use and ask a doctor if

DAYTIME

- nervousness, dizziness, or sleeplessness occur
- symptoms do not get better with 7 days or occur with fever
- cough lasts more than 7 days, comes back, or occurs with a fever, rash, or headache that lasts.These could be signs of a serious condition.

These could be signs of a serious condition.

NIGHTTIME

- nervousness, dizziness, or sleeplessness occur
- pain, nasal congestion, or cough gets worse or lasts more than 5 days
- redness or swelling is present
- new symptoms occur
- fever gets worse or lasts more than 3 days
- cough comes back or occurs with rash or headache that lasts.

These could be signs of a serious condition.

Keep out of reach of children.

Daytime

In case of overdose, get medical help or contact a Poison Control Center (1-800-222-1222) right away.

Nighttime

Overdose warning: Taking more than the recommended dose (overdose) may cause liver damage. In case of overdose, get medical help or contact a Poison Control Center right away (1-800-222-1222). Quick medical attention is critical even if you not notice any signs or symptoms.

Directions

Daytime

- do not take more than 6 doses in any 24-hour period
- use only the enclosed dosing cup designed for use with this product. Do not use any other dosing device.
- keep dosing cup with product
- dose as follows or as directed by a doctor
- mL= milliliter

age | dose
children 6 to under 12 years | 10 mL every 4 hours
children 4 to under 6 years | 5 mL every 4 hours
children under 4 years | do not use

Nighttime

- this product does not contain directions or complete warnings for adult use
- do not give more than directed (see overdose warning)
- do not give more than 5 doses in any 24-hour period
- if needed, repeat dose every 4 hours while symptoms last
- do not give more than 5 days unless directed by a doctor
- measure only with dosing cup provided. Do not use any other dosing device
- mL = milliliter
- dose as follows or as directed by a doctor
- children 6 to under 12 years of age: 10 mL every 4 hours
- children under 6 years of age: do not use

Other information

Daytime

- each 5 mL contains: sodium 5 mg
- store between 20-25ºC (68º-77ºF). Do not refrigerate.

Nighttime

- each 10 mL contains: sodium 6 mg
- store between 20-25ºC (68-77ºF). Do not refrigerate.

Inactive ingredients

Inactive ingredients for Day Time

anhydrous citric acid, EDTA disodium, FD&C red #40, flavor, glycerin, propylene glycol, propyl gallate, purified water, sodium benzoate, sorbitol, sucralose, trisodium citrate dihydrate, xanthan gum

Inactive ingredients for Night Time

anhydrous citric acid, EDTA disdoium, FD&C blue #1, FD&C red #40, flavor, glycerin, propylene glycol, propyl gallate, purified water, sodium benzoate, sorbitol, sucralose, trisodium citrate dihydrate, xanthan gum

Questions or comments?

Call 1-877-753-3935 Monday-Friday 9AM-5PM EST

Principal Display Panel

Compare to the active ingredients in Children's Mucinex DayTime Multi-Symptom Cold & Night Time Multi-Symptom Cold††

Children's

MULTI-SYMPTOM COLD

DEXTROMETHORPAN HBr 5 mg / COUGH SUPPRESSANT

GUAIFENESIN 100 mg / EXPECTORANT

PHENYLEPHRINE HCI 2.5 mg / NASAL DECONGESTANT

DAYTIME

ALCOHOL FREE

- Relief from chest congestion, cough & stuffy nose
- Breaks up mucus

AGES 4 - 11 YEARS

Berry flavor

FL OZ (mL)

children's

MULTI-SYMPTOM

ACETAMINOPHEN 325 mg / PAIN RELIEVER / FEVER REDUCER

DIPHENHYDRAMINE HCI 12.5 mg / ANTIHISTAMINE / COUGH SUPPRESSANT

PHENYLEPHRINE HCI 5 mg / NASAL DECONGESTANT

NIGHTTIME

ALCOHOL FREE

- Relief from stuffy nose, cough, fever, sore throat, runny nose & sneezing

AGES 6 - 11 YEARS

Berry flavor

FL OZ (mL)

TAMPER EVIDENT: DO NOT USE IF PRINTED SAFETY SEAL AROUND BOTTLE OR UNDER CAP IS BROKEN OR MISSING

KEEP OUTER CARTON FOR COMPLETE WARNINGS AND PRODUCT INFORMATION

††This product is not manufactured or distributed by Reckitt Benckiser, distributor of Children's Mucinex® Night Time Multi-Symptom Cold and Children's Mucinex® Multi-Symptom Cold

DISTRIBUTED BY; WALGREEN CO.

200 WILMOT RD., DEERFIELD, IL 60015

walgreens.com

Product Label

WALGREENS Multi-Symptom Children's Cold